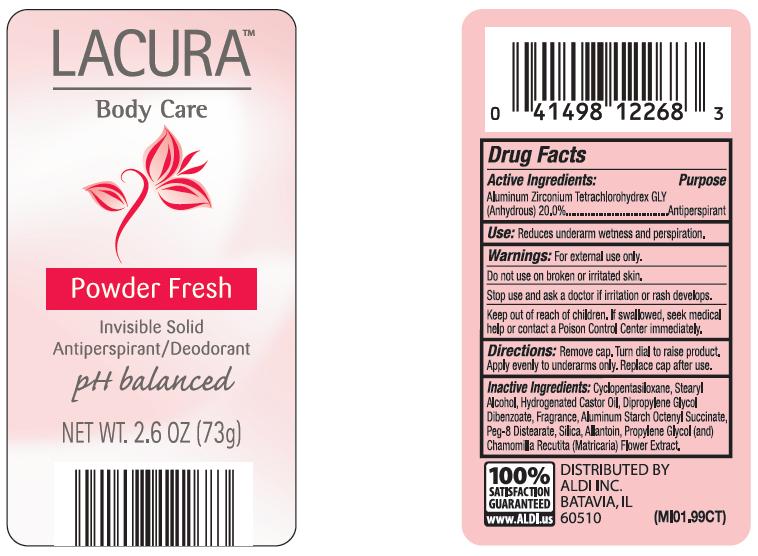 DRUG LABEL: LACURA
NDC: 64024-970 | Form: STICK
Manufacturer: ALDI INC
Category: otc | Type: HUMAN OTC DRUG LABEL
Date: 20101108

ACTIVE INGREDIENTS: ALUMINUM ZIRCONIUM TETRACHLOROHYDREX GLY  200 mg/1 g
INACTIVE INGREDIENTS: CYCLOMETHICONE 5; STEARYL ALCOHOL; HYDROGENATED CASTOR OIL; PEG-8 DISTEARATE; SILICON DIOXIDE; ALUMINUM STARCH OCTENYLSUCCINATE

Drug Facts

Active Ingredients: Aluminum Zirconium Tetrachlorohydrex Gly 20%.

Purpose: Antiperspirant

Warnings:

For external use only.

Do not use on broken or irritated skin.

Stop use and ask a doctor if irritation or rash develops.

DOSAGE AND ADMINISTRATION

Directions:Remove cap. Turn dial to raise product. Apply evenly underarms only. Replace cap after use.

INDICATIONS AND USAGE

Reduces underarm wetness and perspiration

INACTIVE INGREDIENT

Inactive Ingredients:CYCLOPENTASILOXANE, STEARYL ALCOHOL, HYDROGENATED CASTOR OIL,
DIPROPYLENE GLYCOL DIBENZOATE, FRAGRANCE, ALUMINUM STARCH OCTENYL SUCCINATE, PEG-8 DISTEARATE, SILICA, ALLANTION, PROPYLENE GLYCOL (AND) CHAMOMILLA RECUTITA (MATRICARIA) FLOWER EXTRACT.

Keep out of reach of children. If swallowed, seek medical help or contact a Poison Control Center immediately.